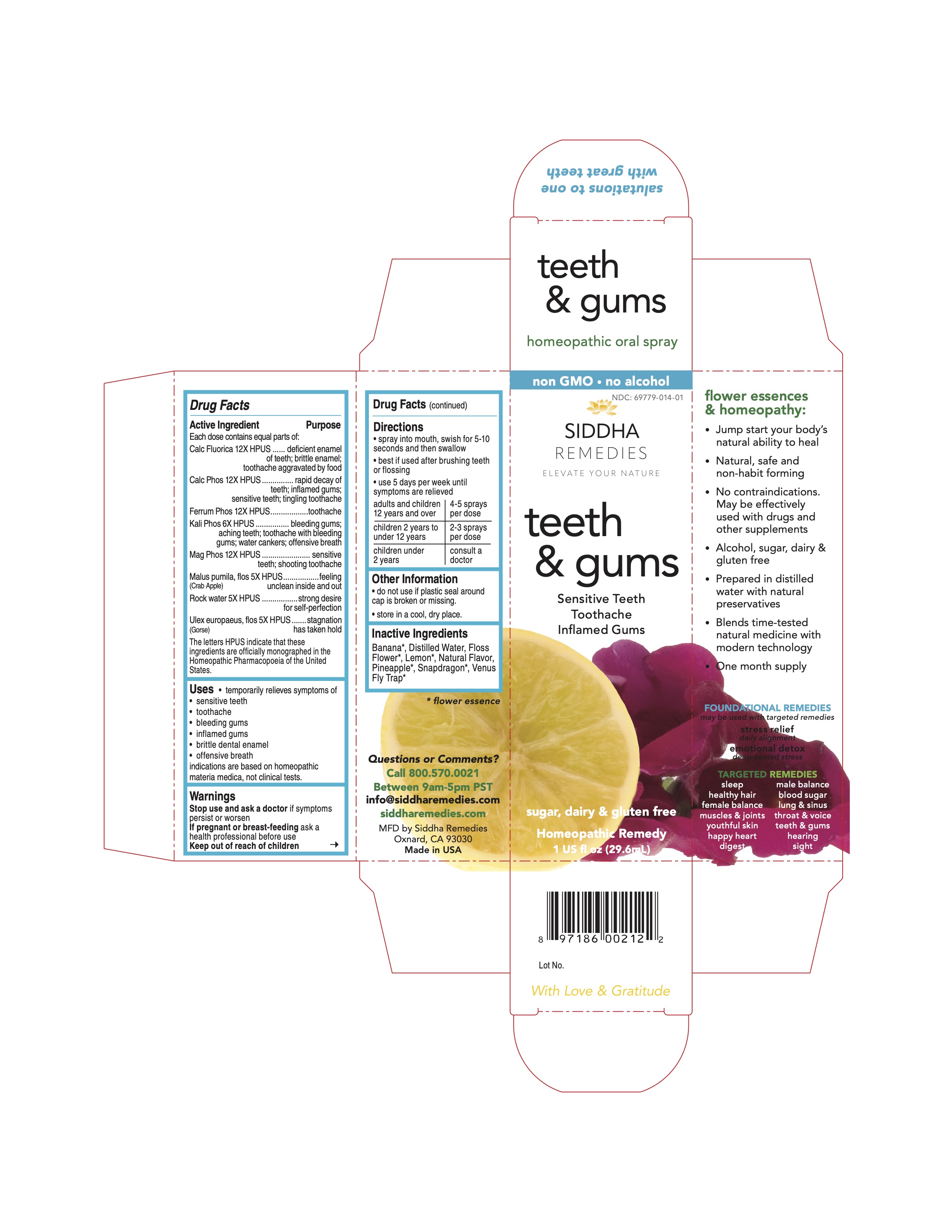 DRUG LABEL: teeth and gums
NDC: 69779-014 | Form: SPRAY
Manufacturer: Siddha Flower Essences LLC
Category: homeopathic | Type: HUMAN OTC DRUG LABEL
Date: 20251231

ACTIVE INGREDIENTS: CALCIUM FLUORIDE 12 [hp_X]/29.6 mL; TRIBASIC CALCIUM PHOSPHATE 12 [hp_X]/29.6 mL; FERROSOFERRIC PHOSPHATE 12 [hp_X]/29.6 mL; POTASSIUM PHOSPHATE, DIBASIC 6 [hp_X]/29.6 mL; MAGNESIUM PHOSPHATE, DIBASIC TRIHYDRATE 12 [hp_X]/29.6 mL; MALUS DOMESTICA FLOWER 5 [hp_X]/29.6 mL; WATER 5 [hp_X]/29.6 mL; ULEX EUROPAEUS FLOWER 5 [hp_X]/29.6 mL
INACTIVE INGREDIENTS: MUSA X PARADISIACA FLOWER; LEMON; PINEAPPLE

Drug Facts

Active Ingredient

Each dose contains equal parts of:

Calc Fluorica 12X HPUS
Calc Phos 12X HPUS
Ferrum Phos 12X HPUS
Kali Phos 6X HPUS
Mag Phos 12X HPUS
Malus pumila, flos (Crab Apple) 5X HPUS
Rock water 5X HPUS
Ulex europaeus, flos (Gorse) 5X HPUS

Purpose

Each dose contains equal parts of:
Calc Fluorica 12X HPUS.................................deficient enamel of teeth; brittle enamel; toothache aggravated by food
Calc Phos 12X HPUS.....................................rapid decay of teeth; inflamed gums; sensitive teeth; tingling toothache
Ferrum Phos 12X HPUS.................................toothache
Kali Phos 6X HPUS.......................................bleeding gums; aching teeth; toothache with bleeding gums; water cankers; offensive breath
Mag Phos 12X HPUS.....................................sensitive teeth; shooting toothache
Malus pumila, flos (Crab Apple) 5X HPUS........feeling unclean inside and out
Rock water 5X HPUS.....................................strong desire for perfection
Ulex europaeus, flos (Gorse) 5X HPUS............stagnation has taken hold
The letters HPUS indicate that these ingredients are officially monographed in the Homeopathic Pharmacopoeia of the United States.

Uses

- temporarily relieves symptoms of
- sensitive teeth
- toothache
- bleeding gums
- inflamed gums
- brittle dental enamel
- offensive breath

indications are based on homeopathic materia medica, not clinical tests

Warnings

Stop use and ask a doctor if symptoms persist or worsen

PREGNANCY OR BREAST FEEDING

If pregnant or breast-feeding ask a health professional before use

Keep out of reach of children

Directions

- spray in mouth, swish for 5-10 seconds and then swallow
- best if used after brushing teeth or flossing
- use 5 days per week until symptoms are relieved

adults and children 12 years and over | 4-5 sprays per dose
children 2 years to under 12 years | 2-3 sprays per dose
children under 2 years | consult a doctor

Other Information

- do not use if plastic seal around cap is broken or missing.
- store in a cool, dry place.

Inactive Ingredients

Banana*, Floss Flower*, Lemon*, Natural Flavor, Pineapple*, Purified Water, Snapdragon*, Venus Fly Trap*

*flower essence

Questions or Comments?
Call 800.570.0021
Between 9am-5pm PST
info@siddhaflowers.com
siddhaflowers.com
MFD by Siddha Flower Essences
Oxnard, CA 93030
Made in USA

Side Panel

flower essences and homeopathy:

- Jump start your body's natural ability to heal
- Natural, safe and non-habit forming
- No contraindications. May be effectively used with drugs and other supplements
- Alcohol, sugar, dairy and gluten free
- Prepared in purified water with natural preservatives
- Blends time-tested natural medicine with modern technology
- One month supply

FOUNDATIONAL REMEDIES
may be used with targeted remedies
stress relief
daily alignment
emotional detox
deep-seated stress
TARGETED REMEDIES
sleep male balance
healthy hair blood sugar
female balance lung and sinus
muscles and joints throat and voice
youthful skin teeth and gums
happy heart hearing
digestion sight

Principal Display Panel

non GMO - no alcohol
siddha cell salts + flower essences
teeth and gums
Sensitive Teeth
Toothache
Inflamed Gums
sugar, dairy and gluten free
Homeopathic Remedy
1 US fl oz (29.6mL)